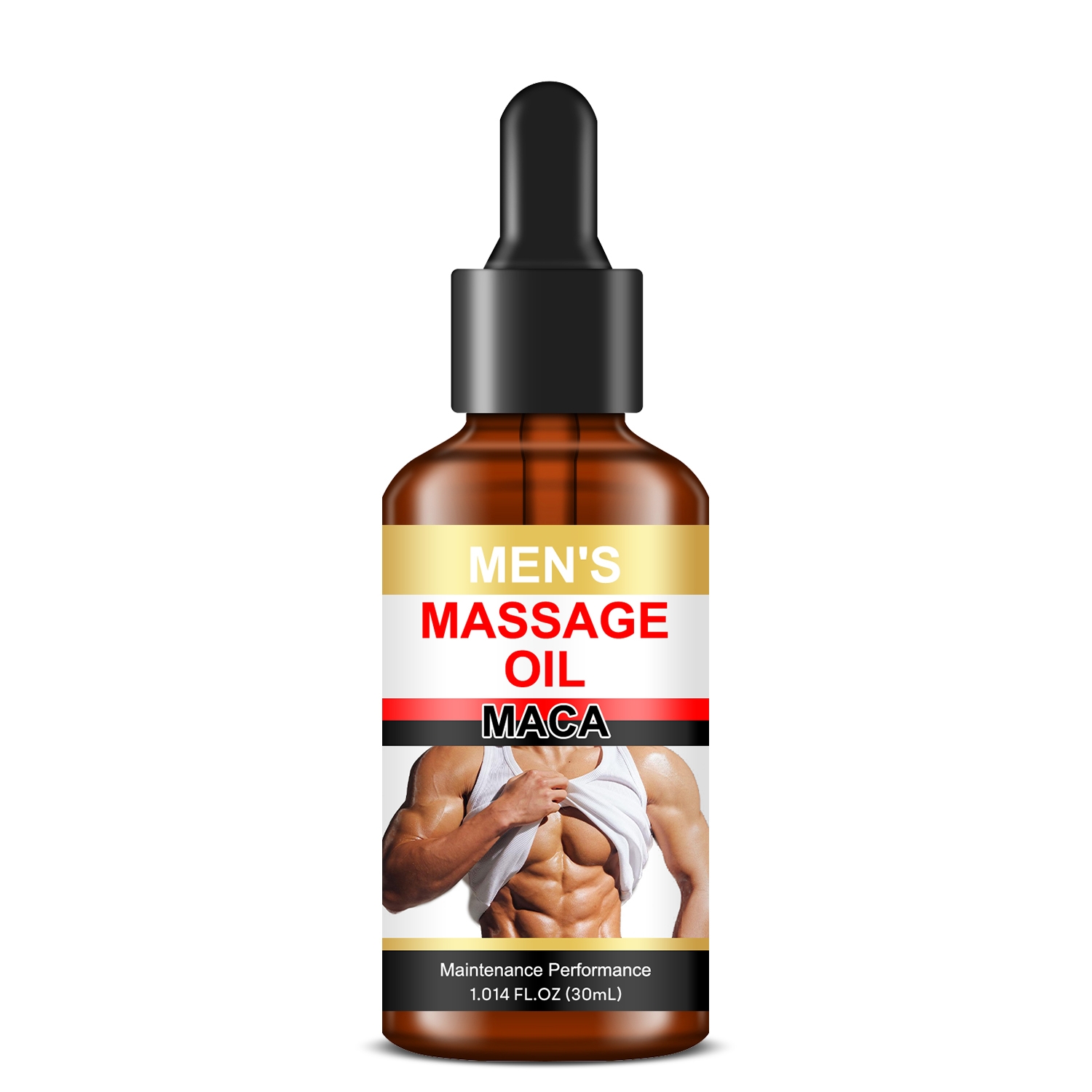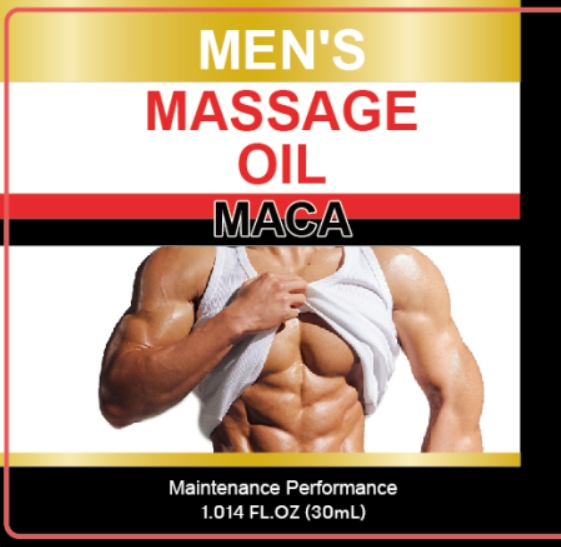 DRUG LABEL: Mens Massage Oil
NDC: 84025-093 | Form: OIL
Manufacturer: Guangzhou Yanxi Biotechnology Co.. Ltd
Category: otc | Type: HUMAN OTC DRUG LABEL
Date: 20240726

ACTIVE INGREDIENTS: PANTHENOL 3 mg/30 mL; GLYCERIN 5 mg/30 mL
INACTIVE INGREDIENTS: WATER

DOSAGE AND ADMINISTRATION

For Men's Daily Skin Care

WARNINGS

Keep out of children

INACTIVE INGREDIENT

Aqua

INDICATIONS AND USAGE

For daily use on men's skin

PURPOSE

Deeply nourishes men's skin and solves the problem of sticky men's skin.

Keep out of children